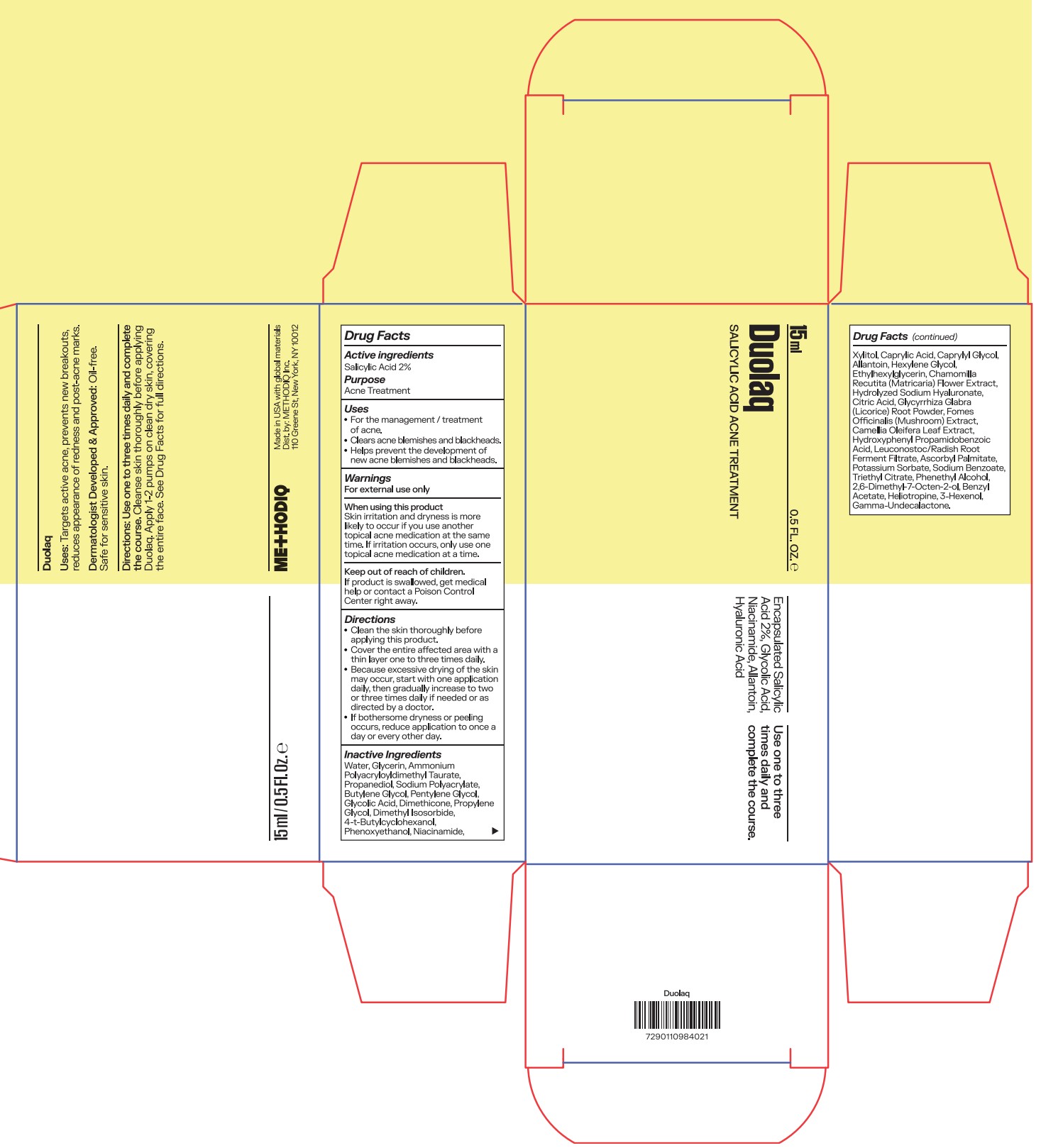 DRUG LABEL: Duolaq
NDC: 87110-001 | Form: GEL
Manufacturer: METHODIQ INC.
Category: otc | Type: HUMAN OTC DRUG LABEL
Date: 20251110

ACTIVE INGREDIENTS: SALICYLIC ACID 20 mg/1 mL
INACTIVE INGREDIENTS: LARICIFOMES OFFICINALIS FRUITING BODY; PENTYLENE GLYCOL; DIMETHYL ISOSORBIDE; 4-T-BUTYLCYCLOHEXANOL; TRIETHYL CITRATE; DIMETHICONE; ALLANTOIN; NIACINAMIDE; GAMMA-UNDECALACTONE; GLYCOLIC ACID; POTASSIUM SORBATE; CAPRYLIC ACID; CAPRYLYL GLYCOL; CHAMOMILE; SODIUM HYALURONATE; CITRIC ACID; HYDROXYPHENYL PROPAMIDOBENZOIC ACID; ASCORBYL PALMITATE; HELIOTROPINE; WATER; GLYCERIN; PHENETHYL ALCOHOL; GLYCYRRHIZA GLABRA (LICORICE) ROOT POWDER; CAMELLIA OLEIFERA LEAF; SODIUM BENZOATE; PROPANEDIOL; 2,6-DIMETHYL-7-OCTEN-2-OL; PROPYLENE GLYCOL; BENZYL ACETATE; XYLITOL; ETHYLHEXYLGLYCERIN; LEUCONOSTOC/RADISH ROOT FERMENT FILTRATE; 3-HEXENOL; AMMONIUM POLYACRYLOYLDIMETHYL TAURATE; SODIUM POLYACRYLATE (8000 MW); BUTYLENE GLYCOL; PHENOXYETHANOL; HEXYLENE GLYCOL

Duolaq

Active ingredients

Salicylic Acid 2%

Purpose

Salicylic Acid 2%................Acne Treatment

Uses

- For the management / treatment of acne.
- Clears acne blemishes and blackheads.
- Helps prevent the development of new acne blemishes and blackheads

Warnings

For external use only

When using this product
Skin irritation and dryness is more likely to occur if you use another topical acne medication at the same time. If irritation occurs, only use one topical acne medication at a time.

Keep out of reach of children.
If product is swallowed, get medical help or contact a Poison Control Center right away.

Directions

- Clean the skin thoroughly before applying this product.
- Cover the entire affected area with a thin layer one to three times daily.
- Because excessive drying of the skin may occur, start with one application daily, then gradually increase to two or three times daily if needed or as directed by a doctor.
- If bothersome dryness or peeling occurs, reduce application to once a day or every other day.

Inactive ingredients

Water, Glycerin, Ammonium Polyacryloyldimethyl Taurate, Propanediol, Sodium Polyacrylate, Butylene Glycol, Pentylene Glycol, Glycolic Acid, Dimethicone, Propylene Glycol, Dimethyl Isosorbide, 4-t-Butylcyclohexanol, Phenoxyethanol, Niacinamide, Xylitol, Caprylic Acid, Caprylyl Glycol, Allantoin, Hexylene Glycol, Ethylhexylglycerin, Chamomilla Recutita (Matricaria) Flower Extract, Hydrolyzed Sodium Hyaluronate, Citric Acid, Glycyrrhiza Glabra (Licorice) Root Powder, Fomes Officinalis (Mushroom) Extract, Camellia Oleifera Leaf Extract, Hydroxyphenyl Propamidobenzoic Acid, Leuconostoc/Radish Root Ferment Filtrate, Ascorbyl Palmitate, Potassium Sorbate, Sodium Benzoate, Triethyl Citrate, Phenethyl Alcohol, 2,6-Dimethyl-7-Octen-2-ol, Benzyl Acetate, Heliotropine, 3-Hexenol, Gamma-Undecalactone.

PACKAGE LABEL

15ml

0.5 Fl. Oz.

Duolaq

Salicylic Acid Acne Treatment